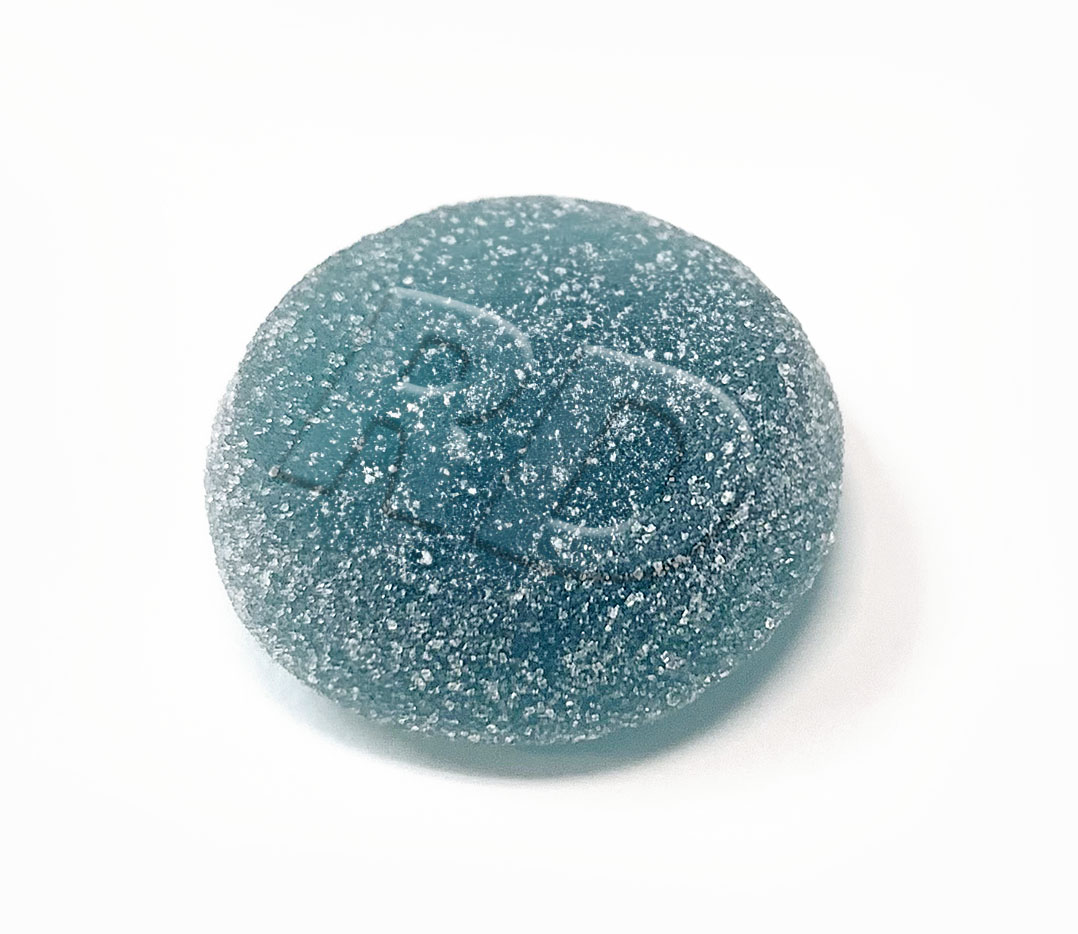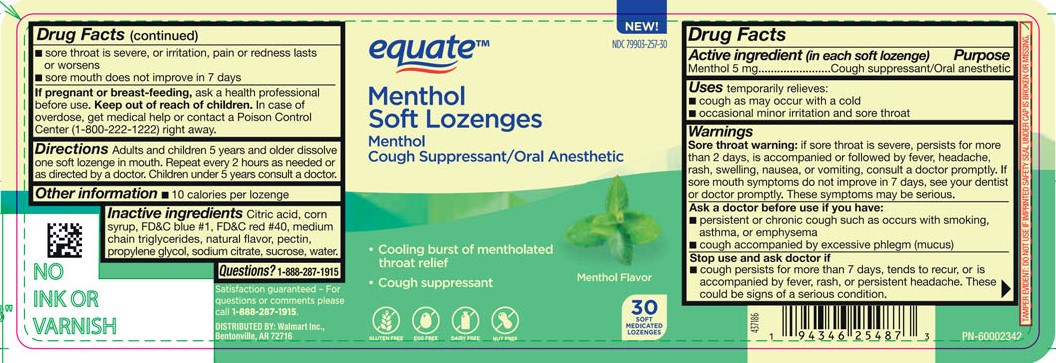 DRUG LABEL: Equate Menthol Chewable Gels
NDC: 79903-257 | Form: CHEWABLE GEL
Manufacturer: Walmart
Category: otc | Type: HUMAN OTC DRUG LABEL
Date: 20251223

ACTIVE INGREDIENTS: MENTHOL 5 mg/1 1
INACTIVE INGREDIENTS: WATER

Menthol 5.0 mg

Active ingredient (in each soft lozenge)

Menthol 5 mg

Purpose

Cough suppressant / Oral anesthetic

INDICATIONS AND USAGE

Uses temporarily relieves:

- cough as may occur with a cold
- occasional minor irritation and sore throat

Warnings

Sore throat warning: if sore throat is severe, persists for more than 2 days, is accompanied or followed by fever, headache, rash, swelling, nausea, or vomiting, consult a doctor promptly. If sore mouth symptoms do not improve in 7 days, see your dentist or doctor promptly. These symptoms may be serious.

Ask a doctor before use if you have:

- persistent or chronic cough such as occurs with smoking, asthma, or emphysema
- cough accompanied by excessive phlegm (mucus)

Stop use and ask doctor if

- cough persists for more than 7 days, tends to recur, or is accompanied by fever, rash, or persistent headache. These could be signs of a serious condition.
- sore throat is severe, or irritation, pain or redness lasts or worsens
- sore mouth does not improve in 7 days

PREGNANCY OR BREAST FEEDING

If pregnant or breast-feeding, ask a health professional before use.

Keep out of reach of children.

OVERDOSAGE

In case of overdose, get medical help or contact a Poison Control Center (1-800-222-1222) right away.

DOSAGE AND ADMINISTRATION

Directions: Adults and children 5 years and older dissolve one soft lozenge in mouth. Repeat every 2 hours as needed or as directed by a doctor. Children under 5 years consult a doctor.

Other information

- 10 calories per lozenge

INACTIVE INGREDIENT

Inactive ingredients: Citric acid, corn syrup, FD&C blue #1, FD&C red #40, medium chain triglycerides, natural flavor, pectin, propylene glycol, sodium citrate, sucrose, water.

Questions? 1-888-287-1915